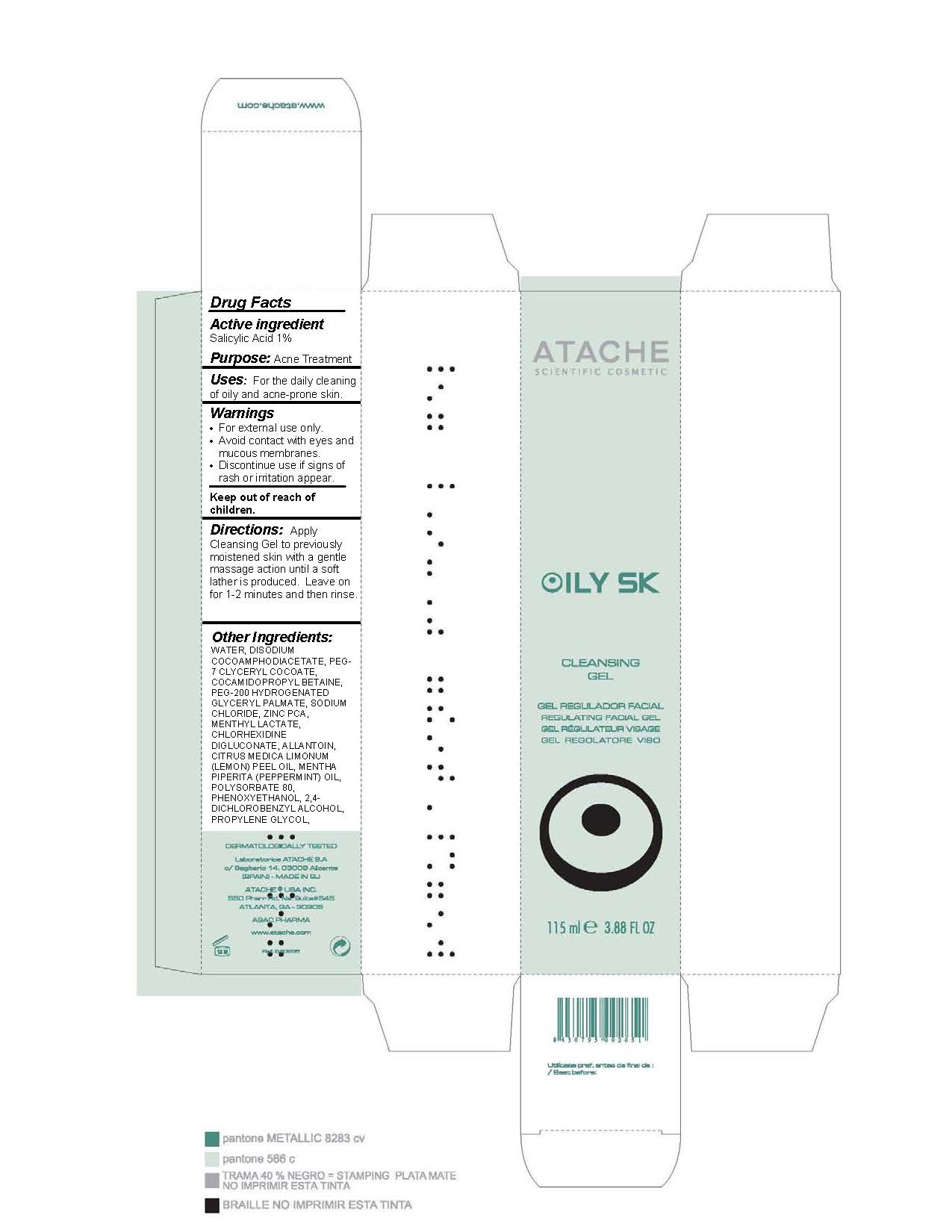 DRUG LABEL: Oily SK Cleansing
NDC: 75870-008 | Form: GEL
Manufacturer: LABORATORIOS DE COSMETICA SCIENTIFICA ATACHE 
Category: otc | Type: HUMAN OTC DRUG LABEL
Date: 20110621

ACTIVE INGREDIENTS: SALICYLIC ACID 1.15 mL/115 mL
INACTIVE INGREDIENTS: WATER; DISODIUM COCOAMPHODIACETATE; COCAMIDOPROPYL BETAINE; POLYETHYLENE GLYCOL 200; SODIUM CHLORIDE; ZINC PIDOLATE; MENTHYL LACTATE; CHLORHEXIDINE GLUCONATE; ALLANTOIN; LEMON OIL; PEPPERMINT OIL; POLYSORBATE 80; PHENOXYETHANOL; PROPYLENE GLYCOL; GLYCERIN

DRUG FACTS

Purpose: Acne Treatment

Active Ingredient:

Salicylic Acid 1%

Keep out of reach of children.

INDICATIONS AND USAGE

Uses: For the daily cleansing of acne and oily-prone skin.

Warnings:

- For external use only.
- Avoid contact with eyes and mucous membranes.
- Discontinue use if signs of irritation or rash appear.

DOSAGE AND ADMINISTRATION

Directions: Apply Cleansing Gel to previously moistened skin with a gentle massage until a soft lather is produced. Leave for 1-2 minutes and then rinse.

INACTIVE INGREDIENT

COSMETIC INGREDIENTS: WATER, DISODIUM COCOAMPHODIACETATE, PEG-7 CLYCERYL COCOATE, COCAMIDOPROPYL BETAINE, PEG-200 HYDROGENATED GLYCERYL PALMATE, SODIUM CHLORIDE, ZINC PCA, MENTHYL LACTATE, CHLORHEXIDINE DIGLUCONATE, ALLANTOIN, CITRUS MEDICA LIMONUM (LEMON) PEEL OIL, MENTHA PIPERITA (PEPPERMINT) OIL, POLYSORBATE 80, PHENOXYETHANOL, 2,4-DICHLOROBENZYL ALCOHOL, PROPYLENE GLYCOL, GLYCERIN.